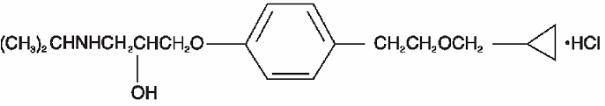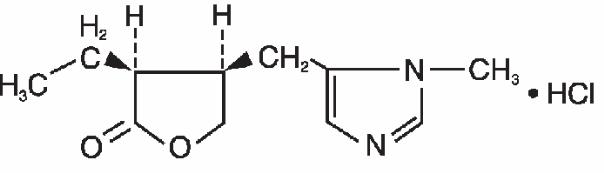 DRUG LABEL: Unknown
Manufacturer: Alcon Laboratories, Inc.
Category: prescription | Type: Human Prescription Drug Label
Date: 20060619

Betoptic®Pilo Ophthalmic
Suspension
(betaxolol 0.25% / pilocarpine
hydrochloride 1.75% ophthalmic
suspension)

DESCRIPTION

Betoptic®Pilo Ophthalmic Suspension contains betaxolol hydrochloride, a cardiovascular (beta1) adrenoceptor antagonist and pilocarpine hydrochloride, a cholinergic parasympathomimetic agent.

Betaxolol hydrochloride is a white, crystalline powder. Its chemical name is (±)-1[p-(cyclopropylmethoxy)ethyl]phenoxy]-3-(isopropylamino)-2-propanol hydrochloride with an empirical formula of C18H29NO3HCl and a molecular weight of 343.89. The chemical structure of betaxolol hydrochloride is as follows:

Pilocarpine hydrochloride is a white powder. Its chemical name is 2(3H)-furanone, 3-ethyldihydro-4-[(1-methyl-1H-imidazol-5-yl)-methyl]-, monohydrochloride, (3S-cis)- with an empirical formula of C11H16N2O2HCl and a molecular weight of 244.72. The chemical structure of pilocarpine hydrochloride is as follows:

Each mL of Betoptic®Pilo Ophthalmic Suspension contains the following:

Active: Betaxolol hydrochloride 2.8 mg equivalent to 2.5 mg betaxolol base and pilocarpine hydrochloride 17.5 mg;

Preservative: Benzalkonium chloride 0.01%.

Inactive: Mannitol, poly(styrene-divinyl benzene) sulfonic acid, carbomer 934P, boric acid, edetate disodium, sodium hydroxide and/or hydrochloric acid to adjust to a pH 6.0-8.0 and purified water.

Betoptic®Pilo Ophthalmic Suspension is provided as a two-part unit for combination by the Pharmacist. It consists of the following components: Part I – a glass syringe containing pilocarpine hydrochloride 8.75%, sodium hydroxide and/or hydrochloric acid (pH 5.0 ± 0.2) and purified water to 1.6 mL; and Part II – a DROP-TAINER® containing betaxolol 0.313%, poly(styrene-divinyl benzene) sulfonic acid, carbomer 934P, boric acid, mannitol, edetate disodium, benzalkonium chloride, sodium hydroxide (pH 8.0 ± 0.2) and purified water to 6.4 mL.

Betoptic®Pilo Ophthalmic Suspension is prepared by affixing a one-inch, blunt, 27 gauge cannula (supplied) to the syringe containing the pilocarpine hydrochloride solution and adding the entire contents of the syringe through the opening in the dropper tip to the DROP-TAINER® containing the betaxolol suspension and mixing well. The final pH of the combination suspension is 6.0 to 8.0

Remove Cap from DropTainer | Add Contents of Syringe through Orifice in DropTainer | Cap and Mix Well. Label with a 2-Week Expiry Period

ADD CONTENTS OF PART I TO PART II AND MIX WELL IMMEDIATELY PRIOR TO DISPENSING AND LABEL WITH A TWO (2) WEEK EXPIRATION DATE

CLINICAL PHARMACOLOGY

Betaxolol hydrochloride, a cardioselective (beta1) adrenoceptor antagonist, does not have significant membrane-stabilizing (local anesthetic) activity and is devoid of intrinsic sympathomimetic action. Orally administered beta-adrenergic blocking agents reduce cardiac output in healthy subjects and subjects with heart disease. In patients with severe impairment of myocardial function, beta-adrenergic receptor antagonists may inhibit the sympathetic stimulatory effect necessary to maintain adequate cardiac function.

Pilocarpine is a direct acting cholinergic parasympathomimetic agent which acts through direct stimulation of muscarinic neuroreceptors and smooth muscle such as the iris and secretory glands. Each of these compounds lowers elevated intraocular pressure (IOP) by different mechanisms of action. Betaxolol lowers IOP predominately by decreasing aqueous humor production. Pilocarpine lowers IOP predominantly by increasing the outflow of aqueous humor from the eye.

The efficacy and safety of Betoptic®Pilo Ophthalmic Suspension dosed TID was evaluated in two prospective, multicenter, controlled clinical trials. In both controlled studies, Betoptic®Pilo Ophthalmic Suspension dosed TID provide up to an additional 1-3 mmHg IOP lowering from the BETOPTIC®-S BID baseline. Betoptic®Pilo has not been shown to be superior to any other beta-blocker aside from Betoptic®-S.

The potential for systemic absorption was evaluated following topical use of Betoptic®Pilo Ophthalmic Suspension TID. After five and eight days of dosing with Betoptic®Pilo Ophthalmic Suspension TID, plasma levels of betaxolol were below the level of quantification (2.0 ng/mL) indicating that TID dosing results in a low systemic exposure to the drug. Plasma concentrations of pilocarpine were higher following topical ocular administration of Pilocarpine HCl Solution 4% QID than after dosing with Betoptic®Pilo Ophthalmic Suspension TID.

INDICATIONS AND USAGE

Betoptic®Pilo Ophthalmic Suspension is indicated for the reduction of elevated intraocular pressure in patients with primary open-angle glaucoma and ocular hypertension who are insufficiently responsive to Betoptic®-S (failed to achieve target IOP determined after multiple measurements over time).

It is not known whether Betoptic®Pilo is equivalent in IOP lowering efficacy to the administration of Betoptic®-S 0.25% and pilocarpine 1.75% dosed separately. It is not known whether Betoptic®Pilo is equivalent to other beta-blockers given in combination with pilocarpine.

CONTRAINDICATIONS

Betoptic®Pilo Ophthalmic Suspension is contraindicated in patients with sinus bradycardia, greater than a first degree atrioventricular heart block, cardiogenic shock or patients with overt cardiac failure.

Betoptic®Pilo Ophthalmic Suspension is also contraindicated in conditions where miosis is undesirable (e.g., peripheral anterior synechia, trauma, acute inflammatory disease of the anterior chamber, glaucoma occurring or persisting after extracapsular cataract extraction when posterior synechia may occur, and papillary block glaucoma).

Hypersensitivity to any component of this product.

WARNINGS

NOT FOR INJECTION OR ORAL ADMINISTRATION. FOR TOPICAL OPHTHALMIC USE ONLY. COMBINE PARTS I AND II PRIOR TO DISPENSING AND LABEL WITH A TWO (2) WEEK EXPIRATION DATE

Topically applied beta-adrenergic blocking agents may be absorbed systemically. The same adverse reactions found with systemic administration of beta-adrenergic blocking agents may occur with topical administration. For example, severe respiratory reactions and cardiac reactions, including death due to bronchospasm in patients with asthma and, rarely, death in association with cardiac failure, have been reported with topical application of beta-adrenergic blocking agents.

Betaxolol has been shown to have a minor effect on heart rate and blood pressure in clinical studies. Caution should be used in treating patients with a history of cardiac failure or heart block. Betoptic®Pilo Ophthalmic Suspension should be discontinued at the first signs of cardiac failure.

PRECAUTIONS

General

Ocular. Pilocarpine-induced miosis may cause difficulty in dark adaptation. Patients should be advised to exercise caution in night driving and hazardous tasks performed in poor illumination.

In patients with angle-closure glaucoma, the immediate treatment objective is to re-open the angle by constriction of the pupil with a miotic agent. Betoptic®Pilo Ophthalmic Suspension contains pilocarpine HCl 1.75%, a miotic, which, while having an effect on the pupil, is unlikely to be sufficient to effectively treat an angle closure event.

Diabetes Mellitus. Beta-adrenergic blocking agents should be administered with caution in patients subject to spontaneous hypoglycemia or to diabetic patients (especially those with labile diabetes) who are receiving insulin or oral hypoglycemic agents. Beta-adrenergic receptor blocking agents may mask the signs of acute hypoglycemia.

Thyrotoxicosis. Beta-adrenergic blocking agents may mask certain clinical signs (e.g., tachycardia) of hyperthyroidism. Patients suspected of developing thyrotoxicosis should be managed carefully to avoid abrupt withdrawal of beta-adrenergic blocking agents, which might precipitate a thyroid storm.

Muscle Weakness. Beta-adrenergic blockage has been reported to potentiate muscle weakness consistent with certain myasthenic symptoms (e.g., diplopia, ptosis and generalized weakness).

Major Surgery. Consideration should be given to the gradual withdrawal of beta-adrenergic blocking agents prior to general anesthesia because of reduced ability of the heart to respond to beta-adrenergically mediated sympathetic reflex stimuli.

Pulmonary. Caution should be exercised in the treatment of glaucoma patients with excessive restriction of pulmonary function. There have been reports of asthmatic attacks and pulmonary distress during betaxolol treatment. Although rechallenges of such patients with ophthalmic betaxolol have not adversely affected pulmonary function test results, the possibility of adverse pulmonary effects in patients sensitive to beta blockers cannot be ruled out.

Risk from Anaphylactic Reaction. While taking beta-blockers, patients with a history of atopy or a history of severe anaphylactic reaction to a variety of allergens may be more reactive to repeated accidental, diagnostic, or therapeutic challenge with such allergens. Such patients may be unresponsive to the usual doses of epinephrine used to treat anaphylactic reactions.

Information for Patients

There have been reports of bacterial keratitis associated with the use of multiple-dose containers of topical ophthalmic products. These containers had been inadvertently contaminated by patients who, in most cases, had a concurrent corneal disease or disruption of the ocular epithelial surface.

The preservative in Betoptic®Pilo, benzalkonium chloride, may be absorbed by soft contact lenses. Betoptic®Pilo should not be administered while wearing soft contact lenses.

Drug Interactions

Patients who are receiving a beta-adrenergic blocking agent orally and Betoptic®Pilo Ophthalmic Suspension should be observed for a potential additive effect on the intraocular pressure or on the known systemic effects of beta blockade.

Close observation of the patient is recommended when a beta blocker is administered to patients receiving catecholamine-depleting drugs (e.g., reserpine) or calcium-channel blockers because of possible additive effects and the production of hypotension or marked bradycardia, which may produce vertigo, syncope, or postural hypotension.

Betaxolol is an adrenergic blocking agent; therefore, caution should be exercised in patients using concomitant adrenergic psychotropic drugs.

Carcinogenesis, Mutagenesis, Impairment of Fertility

Lifetime studies with betaxolol hydrochloride have been completed in mice at oral doses of 6, 20, or 60 mg/kg/day and in rats at 3, 12, or 48 mg/kg/day; betaxolol hydrochloride demonstrated no carcinogenic effect. Higher dose levels were not tested. In a variety of in vitro bacterial and mammalian cell assays, betaxolol hydrochloride was nonmutagenic.

There have been no long-term studies done using pilocarpine in animals to evaluate carcinogenic potential.

Pregnancy

Teratogenic Effects

Pregnancy Category C

Reproduction, teratology, and peri- and postnatal studies have been conducted with orally administered betaxolol HCl in rats and rabbits. There was evidence of drug related post-implantation loss in rabbits and rats at dose levels above 12 mg/kg and 128 mg/kg, respectively. Betaxolol HCl was shown not to be teratogenic, however, and there were no other adverse effects on reproduction at subtoxic dose levels. There are no adequate and well-controlled studies of betaxolol HCl or pilocarpine in pregnant women. Betoptic®Pilo Ophthalmic Suspension should be used during pregnancy only if the potential benefit justifies the potential risk to the fetus.

Nursing Mothers

It is not known whether topical ocular betaxolol, pilocarpine or Betoptic®Pilo Ophthalmic Suspension is excreted in human milk; however, oral betaxolol is excreted in human milk. Because many drugs are excreted in human milk, a decision should be made whether to discontinue nursing or to discontinue Betoptic®Pilo Ophthalmic Suspension usage, taking into account the benefit of the drug to the mother.

Pediatric Use

Safety and effectiveness in pediatric patients have not been established.

ADVERSE REACTIONS

In multi-center controlled clinical trials of Betoptic®Pilo Ophthalmic Suspension the adverse events reported in an approximately 5 to 20% incidence of patients were: headaches, blurred vision, dim vision, abnormal vision, and vitreous disorder.

In the 3-month controlled clinical trials, 12% of patients enrolled on Betoptic®Pilo treatment discontinued the therapy within the first two weeks of treatment because of intolerance due to adverse reactions. In a 24-month long-term safety study, by Month-12, 20% of patients had discontinued and by the Month-24 endpoint, 55% of patients had discontinued Betoptic®Pilo therapy.

The following adverse events were reported at an incidence of 1 to 4% of patients: bronchitis, browache, constipation, dizziness, hyperemia, ocular discomfort, nausea, and pain.

The following adverse events were reported in less than 1% of the patients: abnormal dreams, asthenia, asthma, blepharitis, conjunctival edema, lid erythema, lid margin crusting, lid spasm, palpitation, periorbital edema, photophobia, scotoma, synechiae, and tearing.

In addition, the following adverse events have been associated with ophthalmic formulations containing betaxolol or pilocarpine:

Ocular: Discomfort characterized by burning and stinging upon instillation, ciliary spasm, conjunctival vascular congestion, myopia (especially in younger individuals who have recently started therapy), and reduced visual acuity in poor illumination (frequently experienced by older individuals and individuals with lens opacity), corneal punctate keratitis, itching, dryness of eyes, erythema, inflammation, discharge, ocular pain, decreased visual acuity and crusty lashes. Retinal detachments have been reported with the use of miotics such as pilocarpine and cataracts may occur with prolonged use of pilocarpine.

Additional ocular events reported with other formulations of betaxolol or pilocarpine include allergic reactions, decreased corneal sensitivity, edema, anisocoria, lacrimation, and superficial keratitis (corneal granularity).

Systemic: Cardiovascular; Bradycardia, heart block, and congestive heart failure; Pulmonary; Pulmonary distress characterized by dyspnea, bronchospasm, thickened bronchial secretions, asthma, and respiratory failure; Nervous System; Insomnia, dizziness, vertigo, temporal or supraorbital headaches, depression, lethargy, and increase in signs and symptoms of myasthenia gravis; Other: Hives, toxic epidermal necrolysis, hair loss and glossitis.

Overdosage

No information is available on overdosage of Betoptic®Pilo Ophthalmic Suspension in humans. The symptoms which might be expected with an overdose of a systemically administered beta-1-adrenergic blocking agent are bradycardia, hypotension and acute cardiac failure. Symptoms associated with pilocarpine toxicity include sweating, salivation, gastrointestinal over activity (nausea, vomiting, diarrhea), tremors, bradycardia, hypotension, atrioventricular block, mental status changes, and bronchial constriction (in asthmatic patients).

Dosage and Administration

One or two drops of Betoptic®Pilo Ophthalmic Suspension should be instilled in the affected eye(s) three-times daily.

How Supplied

Betoptic®Pilo Ophthalmic Suspension is supplied as two parts requiring mixing before dispensing. Part I consists of a glass syringe containing pilocarpine hydrochloride sealed in a sterile blister pack also containing a sterile, one inch, blunt, 27 gauge cannula. Part II consists of a DROP-TAINER® containing betaxolol hydrochloride ophthalmic suspension. Once Part I is added into Part II and mixed, the resulting Betoptic®Pilo Ophthalmic Suspension is to be used for no longer than two (2) weeks. At this time, the reconstituted Betoptic®Pilo Ophthalmic Suspension should be replaced.

Storage: Store at 4 – 30°C (40 – 86°F). Shake well before using. Discard reconstituted suspension two (2) weeks after combining.

Caution: Federal (USA) Law Prohibits Dispensing Without a Prescription.

U.S. Patent No’s.: 4,252,984; 4,311,708; 4,342,783; and 4,911,920

March 26, 1997

Alcon®

Alcon Laboratories, Inc.

Fort Worth, Texas 76134